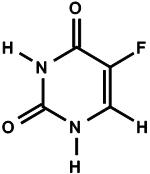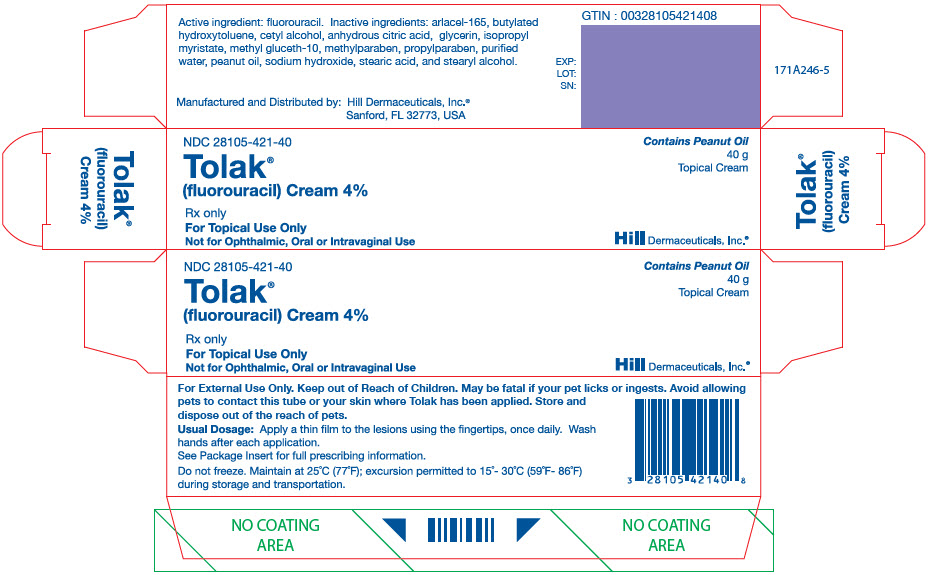 DRUG LABEL: TOLAK
NDC: 28105-421 | Form: CREAM
Manufacturer: HILL DERMACEUTICALS, INC.
Category: prescription | Type: HUMAN PRESCRIPTION DRUG LABEL
Date: 20220906

ACTIVE INGREDIENTS: FLUOROURACIL 0.04 g/1 g
INACTIVE INGREDIENTS: Water; Peanut Oil; Isopropyl Myristate; Methyl Gluceth-10; Glyceryl Monostearate; Polyethylene Glycol 4500; Cetyl Alcohol; Glycerin; Stearyl Alcohol; Stearic acid; Butylated Hydroxytoluene; Methylparaben; Anhydrous Citric Acid; Propylparaben; Sodium Hydroxide

HIGHLIGHTS OF PRESCRIBING INFORMATION

These highlights do not include all the information needed to use TOLAK CREAM safely and effectively. See full prescribing information for TOLAK CREAM.
TOLAK (fluorouracil) Cream, 4%, for topical use
Initial U.S. Approval: 1962

1 INDICATIONS AND USAGE

Tolak (fluorouracil) Cream, 4%, is a nucleoside metabolic inhibitor indicated for the topical treatment of actinic keratosis lesions of the face, ears, and scalp (1).

2 DOSAGE AND ADMINISTRATION

- Apply Tolak Cream after washing, rinsing, and drying the treatment area(s) (2).
- Apply Tolak Cream once daily in an amount sufficient to cover the lesions of the face, ears, and/or scalp with a thin film, using the fingertips to gently massage the medication uniformly into the skin (2).
- Tolak Cream should be applied for a period of 4 weeks as tolerated (2).
- Wash hands thoroughly following Tolak Cream application (2).
- Tolak Cream is for topical use only. Do not apply to eyes, nose, mouth or mucous membranes (2).
- Not for ophthalmic, oral, or intravaginal use (2).

3 DOSAGE FORMS AND STRENGTHS

Cream: 40 mg of fluorouracil per gram of cream (4%) (3).

4 CONTRAINDICATIONS

- Pregnancy (4.1, 8.1).
- Dihydropyrimidine dehydrogenase (DPD) deficiency (4.2).

5 WARNINGS AND PRECAUTIONS

- Application site adverse reactions are likely to occur during and for 4 weeks after treatment of actinic keratosis with Tolak Cream (5.1).
- Hypersensitivity reactions may occur with Tolak Cream (5.2).
- Avoid treatment in the periocular area. Eye disorders, including corneal reactions have occurred with topical fluorouracil use. Avoid accidental transfer of the drug into eyes and to the periocular area. If accidental exposure occurs, seek medical care (5.3).
- Increased sensitivity to ultraviolet light may occur during and immediately after treatment with Tolak Cream (5.4).
- Fluorouracil may cause fetal harm when administered to a pregnant woman. Advise females of reproductive potential to use effective contraception (5.5).
- Increased fluorouracil exposures may occur in DPD deficiency. Discontinue Tolak Cream if symptoms of fluorouracil's systemic toxicity develop (5.6).

6 ADVERSE REACTIONS

The most common (incidence > 68%) adverse reactions occur at the application site and include erythema, scaling/dryness, crusting, pruritus, stinging/burning, edema, and erosions. Erythema is observed in 99% of patients with actinic keratosis treated with Tolak Cream (6.1).

To report SUSPECTED ADVERSE REACTIONS, contact Hill Dermaceuticals at 1-800-344-5707 or FDA at 1-800-FDA-1088 or www.fda.gov/medwatch.

FULL PRESCRIBING INFORMATION

1 INDICATIONS AND USAGE

Tolak (fluorouracil) Cream is indicated for the topical treatment of actinic keratosis lesions of the face, ears, and/or scalp.

2 DOSAGE AND ADMINISTRATION

Prior to application of Tolak Cream, wash, rinse, and dry the treatment areas. Apply Tolak Cream once daily in an amount sufficient to cover the lesions of the face, ears, and/or scalp with a thin film, using the fingertips to gently massage the medication uniformly into the skin. Apply Tolak Cream for a period of 4 weeks as tolerated. Thoroughly wash hands following Tolak Cream application.

Tolak Cream is for topical use only. Do not apply to eyes, nose, mouth or mucous membranes. Not for ophthalmic, oral or intravaginal use.

3 DOSAGE FORMS AND STRENGTHS

Cream: 40 mg of fluorouracil per gram (4%) of white cream in 40 gram tubes.

4 CONTRAINDICATIONS

Tolak Cream is contraindicated:

- During pregnancy [see Warnings and Precautions (5.5, 8.1)]
- In patients with dihydropyrimidine dehydrogenase (DPD) deficiency [see Warnings and Precautions (5.6)]

4.1 Pregnancy

Tolak Cream may cause fetal harm when administered during pregnancy and is contraindicated in women who are pregnant. If this drug is used during pregnancy, or if the patient becomes pregnant while using this drug, the patient should be apprised of the potential hazard to the fetus.

4.2 Dihydropyrimidine Dehydrogenase Deficiency

Tolak Cream is contraindicated in patients with dihydropyrimidine dehydrogenase (DPD) deficiency.

5 WARNINGS AND PRECAUTIONS

5.1 Application Site Adverse Reactions

Application site reactions (erythema, scaling/dryness, edema, crusting, erosions, stinging/burning, and pruritus) were observed in almost all patients during treatment of actinic keratosis on the face, ears, and/or scalp with topical fluorouracil [see Adverse Reactions (6.1)]. In the clinical trials of Tolak Cream, application site irritation returned to baseline (pre-treatment) levels within 4 weeks after discontinuing treatment.

Do not apply Tolak Cream directly into eyes, nose, mouth, or other mucous membranes because irritation, local inflammation and ulceration can occur.

5.2 Hypersensitivity Reactions

Allergic contact dermatitis (delayed type hypersensitivity reaction) has been noted for topical fluorouracil drugs. While application site reactions are observed in almost all patients during treatment of actinic keratosis with topical fluorouracil [see Adverse Reactions (6.2)], delayed type hypersensitivity should be suspected in the event of severe pruritus or eczema at the application site or at a distant site. Although the potential for a delayed hypersensitivity reaction to fluorouracil exists, patch testing to confirm hypersensitivity may be inconclusive.

Tolak Cream contains peanut oil. If signs of hypersensitivity occur, patients should discontinue Tolak Cream immediately and contact their healthcare provider.

5.3 Ophthalmic Adverse Reactions

Corneal and conjunctival disorders have occurred with topical fluorouracil use [see Adverse Reactions (6.2)]. Avoid application to the periocular area. To avoid transfer of the drug into the eyes and to the periocular area during and after application, patients should wash hands well after applying Tolak Cream. If accidental exposure occurs, the patient should flush eye(s) with large amounts of water and seek medical care as soon as possible.

5.4 Photosensitivity

Topical fluorouracil is associated with photosensitivity reactions including severe sunburn. Minimize exposure to ultraviolet rays including sunlight, sun lamps, and tanning beds during and immediately following treatment with Tolak Cream because the intensity of the photosensitivity reaction may be increased.

5.5 Embryofetal Toxicity

Cases of miscarriage and birth defects (including cleft lip and cleft palate) have been reported when pregnant women were exposed to a topical or parenteral fluorouracil product. In addition, ventricular septal defect and cases of miscarriage occurred when pregnant women applied a topical fluorouracil product to mucous membranes (Tolak Cream is not indicated for use on the mucous membrane). Furthermore, fluorouracil interferes with the synthesis of deoxyribonucleic acid (DNA), inhibits the formation of ribonucleic acid (RNA), and provokes unbalanced growth and death of cells. Therefore, Tolak Cream is contraindicated in pregnancy.

Advise females of reproductive potential to use effective contraception during Tolak use and for one month after the last dose of Tolak Cream.

5.6 Toxicity in Patients with Dihydropyrimidine Dehydrogenase Deficiency

Life-threatening systemic toxicity has been reported with the topical use of fluorouracil in a patient with DPD deficiency. Symptoms included severe abdominal pain, bloody diarrhea, vomiting, fever, and chills. Physical examination revealed stomatitis, erythematous skin rash, neutropenia, thrombocytopenia, inflammation of the esophagus, stomach and small bowel.

A large percentage of fluorouracil is catabolized by the DPD enzyme. DPD enzyme deficiency may result in increased availability of fluorouracil to the anabolic pathway, which may lead to increased interference with DNA and RNA synthesis and increased cytotoxic activity and potential toxicities [see Clinical Pharmacology (12.1)]. Therefore, Tolak Cream is contraindicated in patients with DPD deficiency.

Patients should discontinue Tolak Cream if symptoms of fluorouracil's systemic toxicity develop.

6 ADVERSE REACTIONS

The following serious adverse reactions are discussed in more detail in other sections of the labeling:

- Application Site Adverse Reactions [see Warnings and Precautions (5.1)]
- Hypersensitivity Reactions [see Warnings and Precautions (5.2)]
- Ophthalmic Adverse Reactions [see Warnings and Precautions (5.3)]
- Photosensitivity [see Warnings and Precautions (5.4)]
- Embryofetal toxicity [see Warnings and Precautions (5.5)]
- Toxicity in Patients with Dihydropyrimidine Dehydrogenase Deficiency [see Warnings and Precautions (5.6)]

6.1 Clinical Trials Experience

Because clinical trials are conducted under widely varying conditions, adverse reaction rates observed in the clinical trials of a drug cannot be directly compared to rates in the clinical trials of another drug and may not reflect the rates observed in practice.

The data described below reflect exposure to Tolak Cream in 397 subjects with actinic keratosis in vehicle-controlled trials. The population ranged in age from 33 to 94 years, was 80% male, and almost all were Caucasian. Most subjects were treated with Tolak Cream once daily for 4 weeks. Throughout the 4-week treatment and the 4-week post-treatment periods, the trials specifically monitored for adverse reactions related to tolerability, including erythema, scaling/dryness, edema, crusting, erosions, stinging/burning, and pruritus.

The number and percentage of subjects with each of these monitored adverse reactions at one or more post-baseline visit(s) during the clinical trials are shown in Table 1.

Table 1: Incidence of Application Site Adverse Reactions Occurring with 4 Weeks of Tolak Cream Treatment in Clinical Trials 1 and 2
 | Tolak Cream N=397 n (%) |  | Vehicle N=120 n (%)
 | Mild, Moderate or Severe | Severe Only | Mild, Moderate or Severe | Severe Only
Erythema | 394 (99%) | 174 (44%) | 102 (85%) | 0 (0%)
Scaling/ Dryness | 377 (95%) | 94 (24%) | 99 (83%) | 0 (0%)
Crusting | 346 (87%) | 87 (22%) | 46 (38%) | 0 (0%)
Pruritus | 337 (85%) | 65 (16%) | 46 (38%) | 1 (1%)
Stinging/ Burning | 346 (87%) | 101 (25%) | 42 (35%) | 0 (0%)
Edema | 275 (69%) | 30 (8%) | 11 (9%) | 0 (0%)
Erosions | 271 (68%) | 44 (11%) | 14 (12%) | 0 (0%)

In these clinical trials, the intensity of the adverse reactions in subjects using Tolak Cream generally increased over the 4-week treatment period, usually reaching maximal levels at 4 weeks of treatment and then diminishing to baseline levels within 4 weeks after cessation of treatment.

In Trials 1 and 2, 11% of Tolak Cream-treated and 3% of vehicle-treated subjects discontinued treatment because of adverse reactions. Of these subjects, the majority had adverse reactions at the application site. Eye swelling, leading to discontinuation, occurred in one subject with Tolak Cream use.

6.2 Postmarketing Experience

The following adverse reactions have been identified during post-approval use of topical fluorouracil. Because these reactions are reported voluntarily from a population of uncertain size, it is not always possible to reliably estimate their frequency or establish a causal relationship to drug exposure.

Blood and Lymphatic System Disorders: leukocytosis, pancytopenia, thrombocytopenia, eosinophilia, neutrophil toxic granulation

Eye disorders: corneal disorder, conjunctival disorder, eye irritation, conjunctivitis, lacrimation

Gastrointestinal disorders: stomatitis

General Disorders and Administration Site Conditions: medicinal taste

Infections and Infestations: herpes simplex

Neoplasms: chronic lymphocytic leukemia, non-melanoma skin cancer

Nervous system disorders: insomnia, irritability

Psychiatric disorders: emotional distress

Skin and subcutaneous tissue disorders: blistering, allergic contact dermatitis, photosensitivity, pain, scarring, skin irritation, rash, ulceration, hyperpigmentation, alopecia, bullous pemphigoid, ichthyosis, suppuration, swelling, soreness, telangiectasia, tenderness, urticaria

7 DRUG INTERACTIONS

Subjects using systemic steroids, immunosuppressants, and immunomodulators were generally excluded from the clinical studies of Tolak Cream, as were subjects who used retinoids, topical steroids, glycolic acid products, alpha-hydroxy products, and chemical peeling products in the treatment areas. No clinical trials were designed to specifically evaluate drug interactions.

8 USE IN SPECIFIC POPULATIONS

8.1 Pregnancy

TERATOGENIC EFFECTS

Teratogenic Effects: Pregnancy Category X [see Contraindications (4.1)].

Cases of miscarriage and birth defects (including cleft lip and cleft palate) have been reported when pregnant women were exposed to a topical or parenteral fluorouracil product. In addition, ventricular septal defect and cases of miscarriage occurred when pregnant women applied a topical fluorouracil product to mucous membranes (Tolak Cream is not indicated for use on the mucous membrane).

Animal reproduction studies have not been conducted with Tolak Cream. Fluorouracil administered parenterally has been shown to be teratogenic in mice, rats, and hamsters when given at doses equivalent to the usual human intravenous dose. However, the amount of fluorouracil absorbed systemically after topical administration to actinic keratosis is minimal [see Clinical Pharmacology (12.3)]. Fluorouracil exhibited maximum teratogenicity when given to mice as single intraperitoneal injections of 10 to 40 mg/kg on day 10 or 12 of gestation. Similarly, intraperitoneal doses of 12 to 37 mg/kg given to rats between days 9 and 12 of gestation and intramuscular doses of 3 to 9 mg/kg given to hamsters between days 8 and 11 of gestation were teratogenic and/or embryotoxic (i.e., resulted in increased resorptions or embryolethality). In monkeys, divided doses of 40 mg/kg given between days 20 and 24 of gestation were not teratogenic. However, doses higher than 40 mg/kg resulted in spontaneous abortions. Based on the recommended human dose and instructions for use, it is not possible to calculate human dose equivalents for animal exposures in these studies.

8.3 Nursing Mothers

Because many drugs are excreted in human milk and there is some systemic absorption of fluorouracil after topical administration, and because of the potential for serious adverse reactions in nursing infants, a decision should be made whether to discontinue nursing or to discontinue drug use, taking into account the importance of the drug to the mother.

8.4 Pediatric Use

Actinic keratosis is not usually observed in the pediatric population except in the case of rare genetic diseases. Tolak Cream is not intended for use in pediatric patients. Safety and effectiveness in children have not been established.

8.5 Geriatric Use

No dose adjustment is required for elderly patients [see Clinical Studies (14)]. The mean age of the 403 subjects treated with Tolak Cream in the clinical trials was 68 years. Of the Tolak Cream-treated subjects, 61% were 65 and over, while 28% were 75 and over.

No overall differences in safety or effectiveness were observed between these subjects and younger subjects, and other reported clinical experience has not identified differences in responses between the elderly and younger patients, but greater sensitivity of some older individuals cannot be ruled out.

11 DESCRIPTION

Tolak (fluorouracil) Cream, 4% contains 40 mg of fluorouracil per gram of white cream for topical application. It is a nucleoside metabolic inhibitor. Chemically, fluorouracil is 5-fluoro-2,4 (1H,3H)-pyrimidinedione. The molecular formula of 5-fluorouracil is C4H3FN2O2, and its molecular weight is 130.1. Its structural formula is:

Tolak Cream contains the following inactive ingredients: arlacel-165, butylated hydroxytoluene, cetyl alcohol, anhydrous citric acid, glycerin, isopropyl myristate, methyl gluceth-10, methylparaben, propylparaben, purified water, peanut oil, sodium hydroxide, stearic acid, and stearyl alcohol. Tolak Cream formulation has an alkaline pH at 8.3 to 9.2.

12 CLINICAL PHARMACOLOGY

12.1 Mechanism of Action

There is evidence that the metabolism of fluorouracil in the anabolic pathway blocks the methylation reaction of deoxyuridylic acid to thymidylic acid. In this manner, fluorouracil interferes with the synthesis of DNA and to a lesser extent inhibits the formation of RNA. Since DNA and RNA are essential for cell division and growth, the effect of fluorouracil may be to create a thymine deficiency that provokes unbalanced growth and death of the cell. The effects of DNA and RNA deprivation are most marked on those cells that grow more rapidly and take up fluorouracil at a more rapid rate.

12.3 Pharmacokinetics

A systemic absorption study of topically applied Tolak Cream was performed in 21 patients with at least 3 actinic keratosis lesions (4 mm or greater in diameter). The steady state concentration of 5-fluorouracil in plasma was examined at 1, 2, 4, 6, 8, 10, 12, 16, and 24 hours after the last dose of a 4-week regimen in subjects with actinic keratosis after "area application" to area(s) in which actinic keratosis lesions were identified at baseline. Areas were defined as the whole region of the left cheek, right cheek, chin and forehead, bald scalp, and right and left ears, where actinic keratosis was identified at baseline. Thus, for example, if an actinic keratosis lesion was identified on the left cheek, Tolak Cream was to be applied as a thin film to the whole area of the left cheek.

Eight patients had undetectable levels of plasma 5-fluorouracil (the lower limit of quantification was 1.00 ng/ml) in all plasma samples following treatment with Tolak Cream. Among patients with detectable plasma 5-fluorouracil levels, the highest level of plasma 5-fluorouracil was generally observed at 1 hour post-dose. The mean observed maximum concentration (± standard deviation) of plasma 5-fluorouracil was 3.66 (±1.58) ng/mL with the range between 1.11 – 7.35 ng/mL.

The catabolism of 5-fluorouracil results in inactive degradation products (such as CO2, urea, α-fluoro-β-alanine).

13 NONCLINICAL TOXICOLOGY

13.1 Carcinogenesis, Mutagenesis, Impairment of Fertility

Adequate long-term studies in animals to evaluate carcinogenic potential of fluorouracil have not been conducted. Studies with the active ingredient of Tolak, fluorouracil, have shown mutagenic effects in in vitro and in vivo tests and impairment of fertility in in vivo animal studies.

Fluorouracil was positive in three in vitro cell neoplastic transformation assays. In the C3H/10T½ clone 8 mouse embryo cell system, the resulting morphologically transformed cells formed tumors when inoculated into immunosuppressed syngeneic mice.

Although no evidence for mutagenic activity of fluorouracil was observed in 3 studies utilizing the Ames test, mutagenic activity was observed in the survival count rec-assay with Bacillus subtilis and in the Drosophila wing-hair spot test. Fluorouracil produced petite mutations in Saccharomyces cerevisiae and demonstrated positive results in the micronucleus test using bone marrow cells of male mice.

Fluorouracil demonstrated clastogenic activity in vitro in Chinese hamster fibroblasts at concentrations of 1.0 and 2.0 µg/mL and was associated with chromatid gaps, breaks, and exchanges. In human lymphocytes, fluorouracil increased sister chromatid exchange in vitro. Additionally, an increase in numerical and structural chromosome aberrations have been observed in peripheral lymphocytes of patients treated with 5-fluorouracil.

In rats, chromosomal abnormalities and changes in chromosome organization in spermatogonia have been observed after intraperitoneal administration of 125 to 250 mg/kg of fluorouracil. Spermatogonial differentiation was also inhibited and resulted in transient infertility. Fluorouracil was inactive, however, at oral doses of 5 to 80 mg/kg/day in studies with a strain of mouse which is sensitive to the induction of sperm head abnormalities after exposure to a range of chemical mutagens and carcinogens. In female rats, fluorouracil administered intraperitoneally at doses of 25 and 50 mg/kg during the preovulatory phase of oogenesis resulted in a significant reduction in the incidence of fertile matings, a delay in the development of preimplantation and postimplantation embryos, an increased incidence of preimplantation lethality, and an induction of chromosomal anomalies in these embryos. In mice, single intravenous or intraperitoneal injections of fluorouracil were toxic to differentiated spermatogonia and spermatocytes (at 500 mg/kg) and produced abnormalities in spermatids (at 50 mg/kg).

14 CLINICAL STUDIES

The efficacy and safety of Tolak Cream was evaluated in two double-blind multi-center trials (Trial 1 and Trial 2) in subjects with at least 5 visible actinic keratosis lesions on the face, scalp, and/or ears. Subjects applied the assigned medication (Tolak Cream or vehicle placebo) to the face, and/or ears and/or scalp once or twice daily for four weeks as directed. Application of the medication involved field treatment of the whole area of the face and/or ears and/or scalp where actinic keratosis lesions were identified at baseline. Subjects receiving confounding treatments or medications were excluded. The effect of treatment was assessed at 4 weeks post-treatment. Subjects were almost all Caucasian, the mean age was approximately 68 years (range was from 33 to 89 years), and the mean number of actinic keratosis lesions was 14.4 in the Tolak group and 16.2 in the vehicle group in Trial 1, and 19.2 in the Tolak group and 23.2 in the vehicle group in Trial 2.

The number and percentage of subjects with 100% clearing of their actinic keratosis lesions and with at least 75% clearing of their actinic keratosis lesions are shown in Table 2.

Table 2 Subjects with 100% and at least 75% Clearing of Actinic Keratosis Lesions at 4 Weeks Post-Treatment
 | Tolak Cream % (n/N) | Vehicle % (n/N)
Subjects with 100% Clearing of Actinic Keratosis Lesions
Trial 1 | 54% (192/353) | 4% (3/70)
Trial 2 | 24% (12/50) | 4% (2/50)
Subjects with At Least 75% Clearing of Actinic Keratosis Lesions
Trial 1 | 80% (284/353) | 7% (5/70)
Trial 2 | 74% (37/50) | 10% (5/50)

Examination of age (< 68 years versus ≥ 68 years) and gender subgroups did not identify differences in response to Tolak Cream among these subgroups. There were too few non-Caucasian subjects to adequately assess differences in effects among racial subgroups.

After completing Trials 1 and 2, subjects who achieved 100% clearing of actinic keratosis lesions with Tolak Cream treatment were followed for 12 months for lesion recurrence. Table 3 presents the long term outcomes of these 204 subjects.

Table 3 Recurrence of Actinic Keratosis Lesions within 12 Months After Completing Trial 1 or 2
 | Cleared Tolak Subjects N=204
Subjects remained clear 12 months after treatment | 56 (27%)
Subjects with recurrence within 12 months [Subjects who applied other treatments for actinic keratosis were counted as having recurrence.] | 110 (54%)
Subjects with no follow-up | 38 (19%)

16 HOW SUPPLIED / STORAGE AND HANDLING

16.1 How Supplied

Tolak (fluorouracil) Cream, 4% containing 40 mg of fluorouracil per gram of white cream is available in a 40 gram tube (NDC 28105-421-40).

16.2 Storage and Handling

Store at 25°C (77°F), with excursion permitted from 15°C to 30°C (59°F - 86°F) [See USP Controlled Room Temperature]. Do not freeze.

17 PATIENT COUNSELING INFORMATION

Advise the patient to read the FDA-approved patient labeling (Patient Information).

Important Administration Instructions

Advise patients of the following:

- Tolak Cream is for external use only.
- Do not apply to eyes, nose, mouth or mucous membranes.
- Avoid inadvertent transfer of Tolak Cream to other body areas, or to another person.
- Keep out of the reach of children.
- Fluorouracil, including Tolak may be fatal if ingested by pets. Avoid allowing pets to contact the Tolak container or the skin where Tolak has been applied. Store Tolak out of reach of pets. Safely discard or clean any cloth or applicator that may retain Tolak and avoid leaving any residues of Tolak on your hands, clothing, carpeting or furniture.

Instruct patients to do the following:

- Apply after washing, rinsing, and drying the treatment area.
- Wash hands thoroughly after application.

Hypersensitivity Reactions

- Inform patients that Tolak Cream contains peanut oil and that hypersensitivity reactions may occur with its use.
- Inform patients to discontinue Tolak Cream immediately and seek medical attention if signs of severe hypersensitivity occur [see Warnings and Precautions (5.2)].

Ophthalmic Adverse Reactions

- Inform patients that ophthalmic adverse reactions can occur with Tolak Cream use.
- Advise patients that Tolak Cream is not for ophthalmic use.
- Advise patients to avoid application around the eyes.
- If accidental exposure occurs, advise patients to flush eye(s) with large amounts of water and seek medical care [see Warnings and Precautions (5.3)].

Increased Sensitivity to UV Light

- Inform patients that topical fluorouracil is associated with photosensitivity reactions including severe sunburn.
- Advise patients to minimize exposure to sun, sun lamps, and tanning beds while using Tolak Cream.
- Advise patients that sunscreens may be applied after Tolak Cream application [see Warnings and Precautions (5.4)].

Embryofetal Toxicity

- Inform females of reproductive potential of the potential risk to a fetus.
- Advise females of reproductive potential to use effective contraception during and for one month after the last dose of Tolak Cream and to inform their healthcare provider of a known or suspected pregnancy [see Warnings and Precautions (5.5)].

Systemic Toxicity in Patients with DPD deficiency

- Advise patient to stop using Tolak immediately and contact physician if abdominal (stomach) pain, bloody diarrhea, vomiting, fever, and/or chills occur with Tolak Cream use.
- Inform patient that these symptoms could be manifestations of a deficiency in the enzyme dihydropyrimidine dehydrogenase (DPD) [see Warnings and Precautions (5.6)].

Manufactured and Distributed by:
Hill Dermaceuticals, Inc.
Sanford, Florida 32773

PATIENT INFORMATION Tolak (tol lak) (fluorouracil) Cream, 4%

Important: Tolak Cream is for use on skin only (topical). Do not get or apply Tolak Cream on your eyelids or in your eyes, nose, mouth, or in the vagina, because it may cause irritation and swelling in these areas.

What is Tolak Cream?

Tolak Cream is a prescription medicine used to treat skin lesions called actinic keratosis on the face, ears, or scalp.

It is not known if Tolak Cream is safe and effective for use on other areas of the body or to treat problems other than actinic keratosis.

It is not known if Tolak Cream is safe and effective in children.

Who should not use Tolak Cream?

Do not use Tolak Cream if:

- you are pregnant or may become pregnant. Tolak Cream may harm your unborn child. Stop using Tolak Cream and tell your doctor right away if you become pregnant while using Tolak Cream.
- your body does not make enough of (you are deficient in) the enzyme called dihydropyrimidine dehydrogenase (DPD). If you do not have enough of this enzyme, you may get serious side effects if you use Tolak Cream. Symptoms of serious side effects include: stomach-area abdominal pain, bloody diarrhea, vomiting, fever, and chills.

What should I tell my doctor before using Tolak Cream?

Before using Tolak Cream, tell your doctor about all your medical conditions, including if you:

- are allergic to any of the ingredients in Tolak Cream. Tolak Cream contains peanut oil. See the end of this leaflet for a list of all of the ingredients in Tolak Cream.
- are pregnant or plan to become pregnant. See "Who should not use Tolak Cream?"
  - Females who are able to become pregnant should use an effective method of birth control during treatment with Tolak Cream and for one month after the last dose of Tolak Cream. Talk to your doctor about birth control methods that may be right for you during treatment with Tolak Cream.
- are breastfeeding or plan to breastfeed. It is not known if Tolak Cream passes into your breast milk. You and your doctor should decide if you will use Tolak Cream or breastfeed.

How should I use Tolak Cream?

- Use Tolak Cream exactly as prescribed by your doctor.
- Apply Tolak Cream 1 time each day, to the areas of your skin to be treated, for 4 weeks. Apply Tolak Cream as follows:
  - Gently wash, rinse, and pat dry the skin areas to be treated.
  - Apply a thin film of the Tolak Cream to the areas to be treated.
  - Gently massage Tolak Cream evenly into your skin.
  - Avoid contact with other areas of your body, and transfer of Tolak Cream from your body to other people.
  - Wash your hands well after you apply Tolak Cream.

What should I avoid while using Tolak Cream?

- Do not cover the treated areas with an airtight dressing. • Avoid sunlight. Tolak Cream can make your skin sensitive to the sun. You could get severe sunburn. Limit your time in the sun during treatment with Tolak Cream. Talk to your doctor if you get sunburn.
- Do not breast feed or become pregnant while using Tolak. If you do become pregnant, stop using Tolak and tell your doctor right away.
- Tolak may be fatal to your pet if your pet licks or ingests Tolak.
- Avoid allowing pets to contact the Tolak container or your skin where you applied Tolak.
- Store Tolak out of reach of pets.
- Safely discard or clean any cloth or applicator that may have Tolak residue.
- Avoid applying Tolak on your clothing, carpeting, or furniture.
- If your pet starts vomiting or starts having a seizure after your pet licks or ingests Tolak, seek immediate veterinary care for your pet.

What are the possible side effects of Tolak Cream?

Tolak Cream can cause serious side effects:

- Skin reactions including possible allergic reactions. Most people using Tolak Cream get skin reactions in the treated areas. You may get skin reactions such as:
  - redness
  - dryness or scaling
  - crusting
  - itching
  - stinging or burning
  - swelling
  - skin loss (erosion)
- Eye problems. Eye problems have happened with the use of medicines that contain fluorouracil that are applied to the skin. To help prevent getting Tolak Cream in your eyes, or transferring Tolak Cream from another part of your body to your eyes or to another person's eyes:
  - avoid applying Tolak Cream near or around your eyes
  - wash your hands well after you apply Tolak Cream
  If you accidentally get Tolak Cream in your eyes, or if Tolak Cream is accidentally transferred to another person's eyes, flush eyes with large amounts of water and get medical help as soon as possible.
- Tolak Cream can cause serious side effects in people who do not have enough of the enzyme dihydropyrimidine dehydrogenase (DPD). See "Who should not use Tolak Cream?" and "What should I tell my doctor before using Tolak Cream?" Stop using Tolak Cream and call your doctor right away if you get any of the following symptoms during treatment with Tolak Cream:
  - stomach-area (abdominal) pain
  - bloody diarrhea
  - vomiting
  - fever
  - chills

Tell your doctor if you get any of these skin reactions and they are severe or do not go away.

These are not all the possible side effects of Tolak Cream. Call your doctor for medical advice about side effects. You may report side effects to FDA at 1-800-FDA-1088.

How should I store Tolak Cream?

- Store Tolak Cream between 68°F to 77°F (20°C to 25°C).
- Do not freeze Tolak Cream.
- Do not use Tolak Cream after the expiration date printed on the tube.

Keep Tolak Cream and all medicines out of the reach of children.

General information about the safe and effective use of Tolak Cream

Medicines are sometimes prescribed for purposes other than those listed in a Patient Information leaflet. Do not use Tolak Cream for a condition for which it was not prescribed. Do not give Tolak Cream to other people, even if they have the same symptoms that you have. It may harm them.

You can ask your pharmacist or doctor for information about Tolak Cream that is written for health professionals.

What are the ingredients in Tolak Cream?

Active ingredient: fluorouracil

Inactive ingredients: arlacel-165, butylated hydroxytoluene, cetyl alcohol, anhydrous citric acid, glycerin, isopropyl myristate, methyl gluceth-10, methylparaben, propylparaben, purified water, peanut oil, sodium hydroxide, stearic acid, and stearyl alcohol.

Manufactured and Distributed by: Hill Dermaceuticals, Inc. Sanford, Florida 32773

For more information, go to www.hillderm.com or call 1-800-344-5707.

This Patient Information has been approved by the U.S. Food and Drug Administration.
Issued: August 2022

PRINCIPAL DISPLAY PANEL - 40 g Tube Carton

NDC 28105-421-40

Tolak®
(fluorouracil) Cream 4%

Rx only

For Topical Use Only
Not for Ophthalmic, Oral or Intravaginal Use

Contains Peanut Oil

40 g

Topical Cream

Hill Dermaceuticals, Inc.®